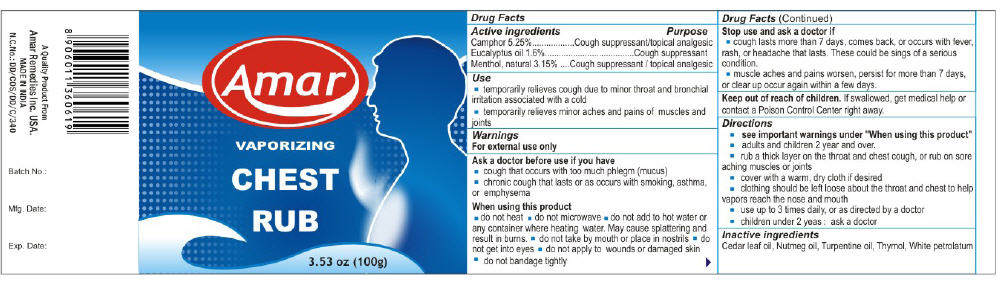 DRUG LABEL: Amar Vaporizing Chest Rub
NDC: 41499-122 | Form: OINTMENT
Manufacturer: Amar Remedies Limited - Mumbai
Category: otc | Type: HUMAN OTC DRUG LABEL
Date: 20110329

ACTIVE INGREDIENTS: Camphor (Synthetic) 5.25 g/100 g; Eucalyptus Oil 1.6 g/100 g; Menthol 3.15 g/100 g
INACTIVE INGREDIENTS: Nutmeg Oil 0.6 g/100 g; Turpentine; Petrolatum

Amar
VAPORIZING
CHEST
RUB

Drug Facts

ACTIVE INGREDIENT

Active ingredients | Purpose
Camphor 5.25% | Cough suppressant/topical analgesic
Eucalyptus oil 1.6% | Cough suppressant
Menthol, natural 3.5% | Cough suppressant / topical analgesic

Use

- temporarily relieves cough due to minor throat and bronchial irritation associated with a cold
- temporarily relieves minor aches and pains of muscles and joints

Warnings

For external use only

Ask a doctor before use if you have

- cough that occurs with too much phlegm (mucus)
- chronic cough that lasts or as occurs with smoking, asthma, or emphysema

When using this product

- do not heat
- do not microwave
- do not add to hot water or any container where heating water. May cause splattering and result in burns.
- do not take by mouth or place in nostrils
- do not get into eyes
- do not apply to wounds or damaged skin
- do not bandage tightly

Stop use and ask a doctor if

- cough lasts more than 7 days, comes back, or occurs with fever, rash, or headache that lasts. These could be sings of a serious condition.
- muscle aches and pains worsen, persist for more than 7 days, or clear up occur again within a few days.

Keep out of reach of children. If swallowed, get medical help or contact a Poison Control Center right away.

Directions

- see important warnings under "When using this product"
- adults and children 2 year and over.
- rub a thick layer on the throat and chest cough, or rub on sore aching muscles or joints
- cover with a warm, dry cloth if desired
- clothing should be left loose about the throat and chest to help vapors reach the nose and mouth
- use up to 3 times daily, or as directed by a doctor
- children under 2 yeas : ask a doctor

Inactive ingredients

Cedar leaf oil, Nutmeg oil, Turpentine oil, Thymol, White petrolatum

PRINCIPAL DISPLAY PANEL - 100g Jar Label

Amar

VAPORIZING
CHEST
RUB

3.53 oz (100g)